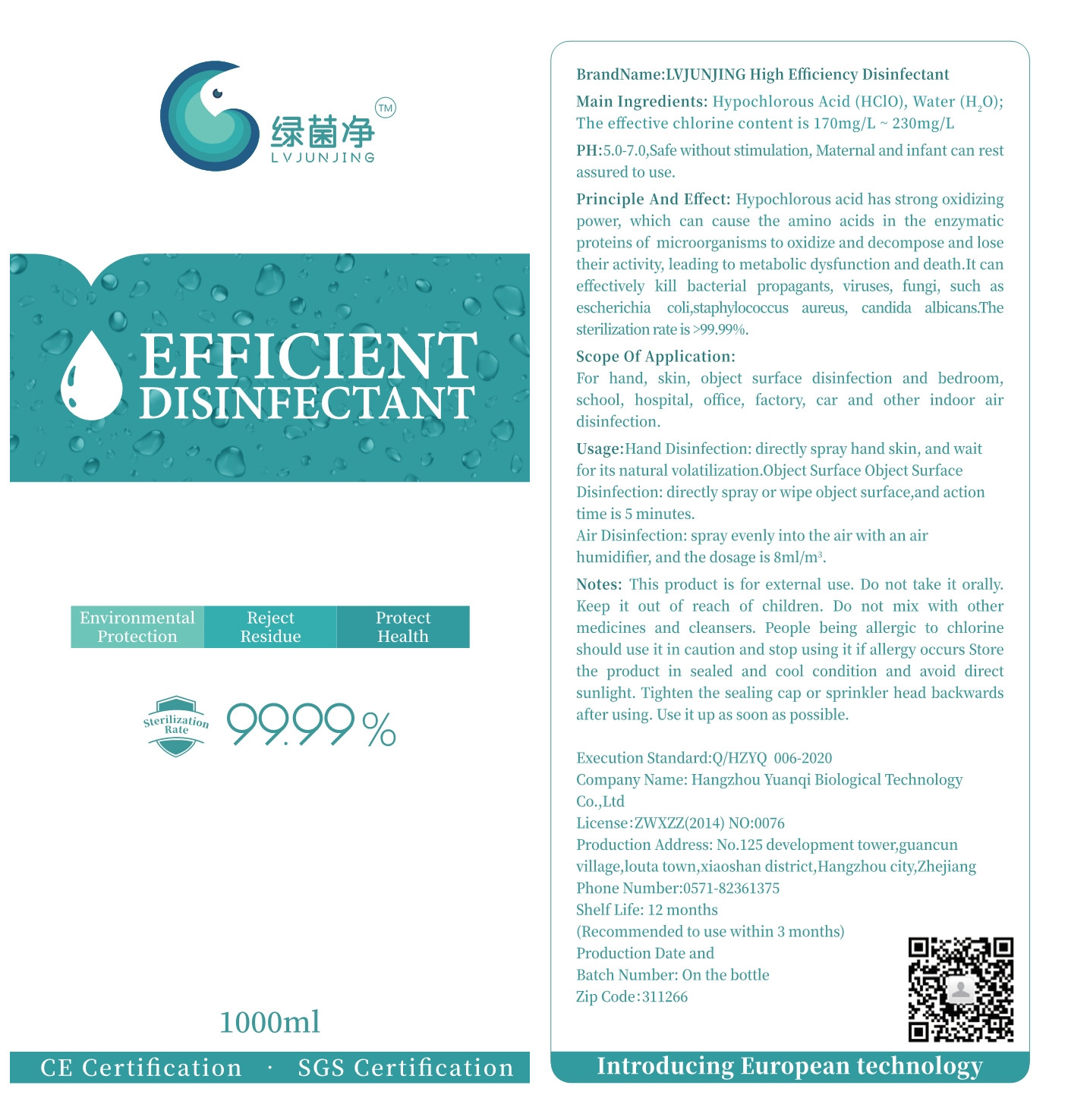 DRUG LABEL: High Efficiency Disinfectant
NDC: 56043-002 | Form: LIQUID
Manufacturer: HANGZHOU YUANQI BIOLOGICAL TECHNOLOGY CO., LTD.
Category: otc | Type: HUMAN OTC DRUG LABEL
Date: 20200508

ACTIVE INGREDIENTS: HYPOCHLOROUS ACID 0.2 g/1000 mL
INACTIVE INGREDIENTS: WATER

DOSAGE AND ADMINISTRATION

Store the product in sealed and cool condition and avoid direct sunlight.

INACTIVE INGREDIENT

WATER

INDICATIONS AND USAGE

1.Hand Disinfection: directly spray hand skin, and wait for its natural volatilization.Object Surface.

2.Object Surface Disinfection: directly spray or wipe object surface,and action time is 5 minutes.
3.Air Disinfection: spray evenly into the air with an air humidifer, and the dosage is 8ml/m'.

ACTIVE INGREDIENT

Hypochlorous acid

keep out of reach of children

PURPOSE

Disinfection
Sterilization
No Rinseing

WARNINGS

This product is for external use. Do not take it orally. Keep it out of reach of children.Do not mix with other medicines and cleansers.
People being allergic to chlorine should use it in caution and stop usingit if allergy occurs Store the product in sealed and cool condition and avoid direct sunlight.Tighten the sealing cap or sprinkler head backwards after using. Use it up as soon as possible.